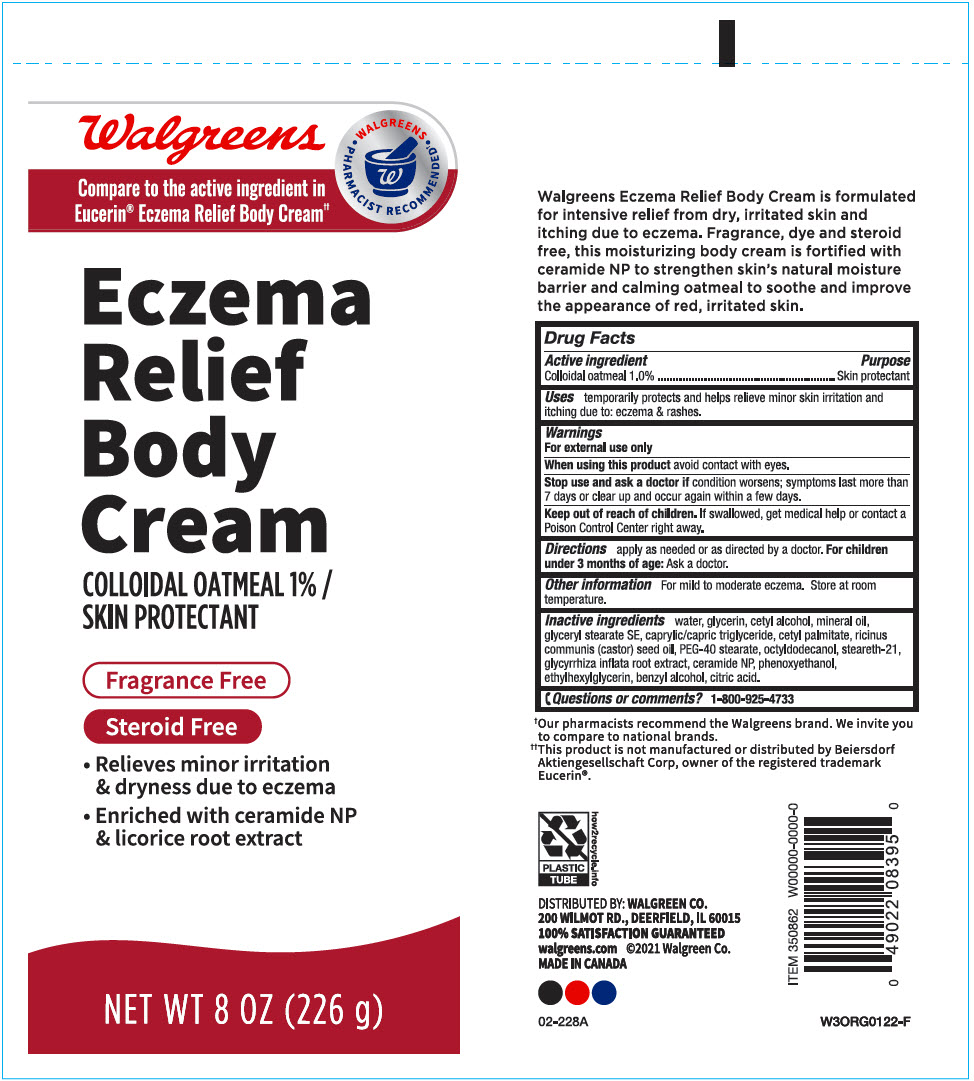 DRUG LABEL: Walgreens Eczema Relief Body
NDC: 0363-8395 | Form: CREAM
Manufacturer: Walgreen Company
Category: otc | Type: HUMAN OTC DRUG LABEL
Date: 20241105

ACTIVE INGREDIENTS: OATMEAL 10 mg/1 g
INACTIVE INGREDIENTS: Water; Glycerin; Cetyl Alcohol; Mineral Oil; Glyceryl Stearate SE; MEDIUM-CHAIN TRIGLYCERIDES; Cetyl Palmitate; CASTOR OIL; PEG-40 MONOSTEARATE; Octyldodecanol; Steareth-21; GLYCYRRHIZA INFLATA ROOT; Ceramide NP; Phenoxyethanol; Ethylhexylglycerin; Benzyl Alcohol; CITRIC ACID MONOHYDRATE

Walgreens Eczema Relief Body Cream
Skin Protectant

Drug Facts

Active ingredient

Colloidal oatmeal 1.0%

Purpose

Skin protectant

Uses

temporarily protects and helps relieve minor skin irritation and itching due to: eczema & rashes

Warnings

For external use only

When using this product avoid contact with eyes.

Stop use and ask a doctor if condition worsens; symptoms last more than 7 days or clear up and occur again within a few days.

Keep out of reach of children. If swallowed, get medical help or contact a Poison Control Center right away.

Directions

apply as needed or as directed by a doctor. For children under 3 months of age: Ask a doctor.

Other information

For mild to moderate eczema. Store at room temperature.

Inactive ingredients

water, glycerin, cetyl alcohol, mineral oil, glyceryl stearate SE, caprilic/capric triglyceride, cetyl palmitate, ricinus communis (castor) seed oil, PEG-40 stearate, octyldodecanol, steareth-21, glycyrrhiza inflate root extract, ceramide NP, phenoxyethanol, ethylhexylglycerin, benzyl alcohol, citric acid.

Questions or comments?

1-800-925-4733

DISTRIBUTED BY: WALGREEN CO.
200 WILMOT RD., DEERFIELD, IL 60015

PRINCIPAL DISPLAY PANEL - 226 g Tube Label

Walgreens

•Walgreens•
PHARMACIST RECOMMENDED†

Compare to the active ingredient in
Eucerin® Eczema Relief Body Cream††

Eczema
Relief
Body
Cream

COLLOIDAL OATMEAL 1% /
SKIN PROTECTANT

Fragrance Free

Steroid Free

- Relieves minor irritation
  & dryness due to eczema
- Enriched with ceramide NP
  & licorice root extract

NET WT 8 OZ (226 g)